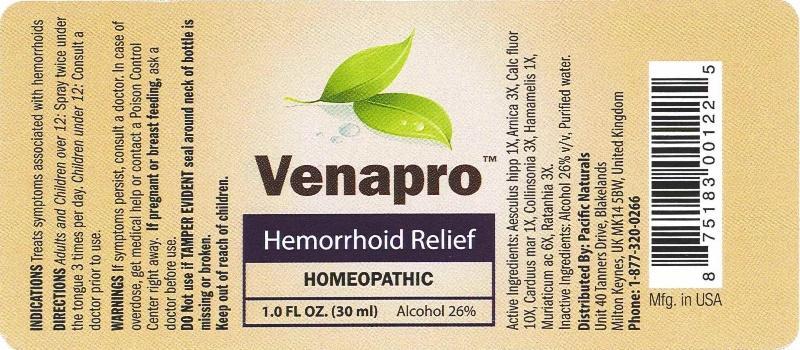 DRUG LABEL: Venapro
NDC: 43695-0003 | Form: SPRAY
Manufacturer: Pacific Naturals
Category: homeopathic | Type: HUMAN OTC DRUG LABEL
Date: 20150202

ACTIVE INGREDIENTS: HORSE CHESTNUT 1 [hp_X]/1 mL; ARNICA MONTANA 3 [hp_X]/1 mL; CALCIUM FLUORIDE 10 [hp_X]/1 mL; MILK THISTLE 1 [hp_X]/1 mL; COLLINSONIA CANADENSIS ROOT 3 [hp_X]/1 mL; HAMAMELIS VIRGINIANA ROOT BARK/STEM BARK 1 [hp_X]/1 mL; HYDROCHLORIC ACID 6 [hp_X]/1 mL; KRAMERIA LAPPACEA ROOT 3 [hp_X]/1 mL
INACTIVE INGREDIENTS: WATER; ALCOHOL

Drug Facts:

ACTIVE INGREDIENTS:

Aesculus hippocastanum 1X, Arnica montana 3X, Calcarea fluorica 10X, Carduus marianus 1X, Collinsonia canadensis 3X, Hamamelis virginiana 1X, Muriaticum acidum 6X, Ratanhia 3X

INDICATIONS:

Treats symptoms associated with hemorrhoids.

WARNINGS:

If symptoms persist, consult a doctor.

In case of overdose, get medical help or contact a Poison Control Center right away.

If pregnant or breast feeding, ask a doctor before use.

DO NOT use if TAMPER EVIDENT seal around neck of bottle is missing or broken.

Keep out of reach of children.

Keep out of reach of children. In case of overdose, get medical help or contact a Poison Control Center right away.

DIRECTIONS:

Adults and Children over 12: Spray twice under the tongue 3 times per day.

Children under 12: Consult a doctor prior to use.

INDICATIONS:

Treats symptoms associated with hemorrhoids.

INACTIVE INGREDIENTS:

Alcohol 26% v/v, Purified water.

QUESTIONS:

Distributed By: Pacific Naturals

Unit 40 Tanners Drive, Blakelands

Milton Keynes, UK MK14 5BW, United Kingdom

Phone: 1-877-320-0266

PACKAGE LABEL DISPLAY:

Venapro

Hemorrhoid Relief

HOMEOPATHIC

1.0 FL OZ. (30 ml)